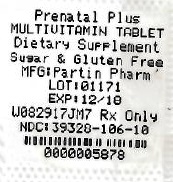 DRUG LABEL: Prenatal Vitamins Plus Low Iron
NDC: 68151-5878 | Form: TABLET
Manufacturer: Carilion Materials Management
Category: prescription | Type: HUMAN PRESCRIPTION DRUG LABEL
Date: 20171226

ACTIVE INGREDIENTS: VITAMIN A ACETATE 3080 [iU]/1 1; .BETA.-CAROTENE 920 [iU]/1 1; ASCORBIC ACID 120 mg/1 1; CHOLECALCIFEROL 400 [iU]/1 1; .ALPHA.-TOCOPHEROL ACETATE, DL- 22 mg/1 1; THIAMINE 1.84 mg/1 1; RIBOFLAVIN 3 mg/1 1; NIACIN 20 mg/1 1; PYRIDOXINE HYDROCHLORIDE 10 mg/1 1; FOLIC ACID 1 mg/1 1; CYANOCOBALAMIN 12 ug/1 1; CALCIUM CARBONATE 200 mg/1 1; IRON 27 mg/1 1; ZINC 25 mg/1 1; COPPER 2 mg/1 1
INACTIVE INGREDIENTS: ASCORBYL PALMITATE; ANHYDROUS CITRIC ACID; .ALPHA.-TOCOPHEROL, DL-; ETHYLCELLULOSE, UNSPECIFIED; FD&C BLUE NO. 2; FD&C RED NO. 40; FD&C YELLOW NO. 6; DEXTROSE, UNSPECIFIED FORM; ACACIA; HYPROMELLOSE, UNSPECIFIED; MAGNESIUM STEARATE; STARCH, CORN; MALTODEXTRIN; METHYLCELLULOSE (100 MPA.S); MICROCRYSTALLINE CELLULOSE; MINERAL OIL; GLYCERYL MONOSTEARATE; POLYETHYLENE GLYCOL, UNSPECIFIED; SILICON DIOXIDE; SORBIC ACID; SOY PROTEIN; STEARIC ACID; SUCROSE; TITANIUM DIOXIDE; TRICALCIUM PHOSPHATE

PRENATAL VITAMINS PLUS LOW IRON TABLETS

DO NOT USE IF IMPRINTED SAFETY SEAL UNDER CAP IS BROKEN OR MISSING

DESCRIPTION

Each Tablet Contains: | Amount Per Tablet | % Daily Value
Vitamin A (from Acetate and Beta Carotene) | 4000 IU | 80%
Vitamin C (Ascorbic Acid) | 120 mg | 200%
Vitamin D-3 (Cholecalciferol) | 400 IU | 100%
Vitamin E (dl-Alpha Tocopheryl Acetate) | 22 mg | 73%
Vitamin B-1(Thiamine Mononitrate) | 1.84 mg | 123%
Vitamin B-2 (Riboflavin) | 3 mg | 176%
Niacin (as Niacinamide) | 20 mg | 100%
Vitamin B-6 (Pyridoxine HCI) | 10 mg | 500%
Folic Acid | 1 mg | 200%
Vitamin B-12 (Cyanocobalamin) | 12 mcg | 200%
Calcium (from Calcium Carbonate) | 200 mg | 20%
Iron (Ferrous Fumarate) | 27 mg | 150%
Zinc (Zinc Oxide) | 25mg | 167%
Copper (Cupric Oxide) | 2 mg | 100%

Other Ingredients: Ascorbyl Palmitate, Citric Acid anhydrous, DL- alpha Tocopherol, Ethylcellulose, FD&C Blue #2 lake, FD&C Red #40 lake, FD&C Yellow #6 lake, Glucose, Gum Acacia, Hypromellose, Magnesium Stearate, Maize Starch, Maltodextrin, Methylcellulose, Microcrystalline Cellulose, Mineral Oil, Mono and di-glycerides, Polyethylene Glycol, Pregelatinzed Corn Starch, Silicon Dioxide, Sorbic Acid, Soy Protein, Stearic Acid, Sucrose, Titanium Dioxide, Tricalcium Phosphate.

INDICATIONS AND USAGE

Indications: To provide Vitamin and Mineral supplementation throughout pregnancy and during the postnatal period for both the lactating and nonlactating mother. It is also useful for improving nutritional status prior to conception.

DOSAGE AND ADMINISTRATION

Directions: Before, during and after pregnancy, one tablet daily or as directed by a physician.

CONTRAINDICATIONS

Contraindications: This product is contraindicated in patients with a known hypersensitivity to any of the ingredients.

PRECAUTIONS

Caution: Folic Acid may partially correct the hematological damage due to Vitamin B-12 deficiency of pernicious anemia while the associated neurological damage progresses.

BOXED WARNING

WARNING: Accidental overdose of iron-containing products is a leading cause of fatal poisoning in children under six. KEEP THIS PRODUCT OUT OF REACH OF CHILDREN. In case of accidental overdose, call a physician or Poison Control Center immediately.

STORAGE AND HANDLING

Store at room temperature, USP. Dispense in a well closed light resistant container.

HOW SUPPLIED

Product: 68151-5878

NDC: 68151-5878-1 1 TABLET in a BLISTER PACK